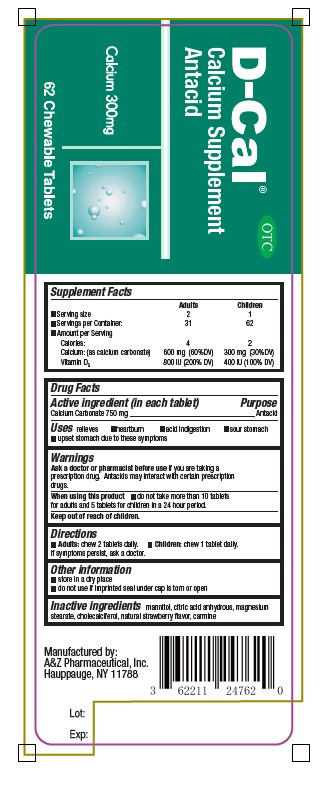 DRUG LABEL: D-CAL
NDC: 62211-247 | Form: TABLET, CHEWABLE
Manufacturer: A&Z Pharmaceutical Inc.
Category: otc | Type: HUMAN OTC DRUG LABEL
Date: 20251201

ACTIVE INGREDIENTS: CALCIUM CARBONATE 750 mg/1 1
INACTIVE INGREDIENTS: MANNITOL; ANHYDROUS CITRIC ACID; MAGNESIUM STEARATE; CHOLECALCIFEROL; STRAWBERRY; CARMINIC ACID

D-CAL (calcium carbonate) tablet, chewable

Supplement Facts

 | Adults | Children
- Serving size | 2 | 1
- Servings per Container: | 31 | 62
- Amount per Serving
Calories:; Calcium: (as calcium carbonate); Vitamin D3 | 4; 600 mg (60%DV); 800 IU (200% DV) | 2; 300 mg (30%DV); 400 IU (100% DV)

Drug Facts

Active ingredient (in each tablet)

Calcium Carbonate 750 mg

Purpose

Antacid

Uses

relieves

- heartburn
- acid indigestion
- sour stomach
- upset stomach due to these symptoms

Warnings

Ask a doctor or pharmacist before use if you are taking a prescription drug. Antacids may interact with certain prescription drugs.

When using this product

- do not take more than 10 tablets for adults and 5 tablets for children in a 24 hour period.

Keep out of reach of children.

Directions

- Adults: chew 2 tablets daily.
- Children: chew 1 tablet daily. If symptoms persist, ask a doctor.

Other information

- Store in a dry place
- do not use if imprinted seal under cap is torn or open

Inactive ingredients

mannitol, citric acid anhydrous, magnesium stearate, cholecalciferol, natural strawberry flavor, carmine

HOW SUPPLIED

Manufactured by:
A&Z Pharmaceutical, Inc.
Hauppauge, NY 11788